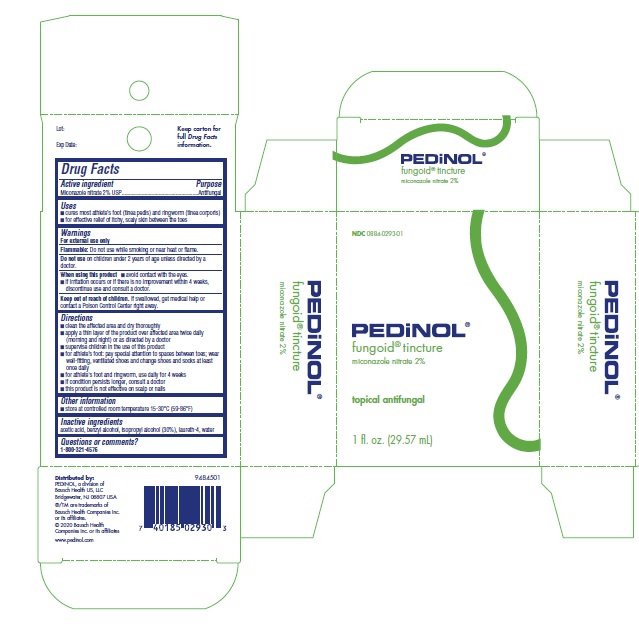 DRUG LABEL: fungoid tincture
NDC: 0884-0293 | Form: TINCTURE
Manufacturer: Pedinol Pharmacal, Inc.
Category: otc | Type: HUMAN OTC DRUG LABEL
Date: 20241017

ACTIVE INGREDIENTS: MICONAZOLE NITRATE 20 mg/1 mL
INACTIVE INGREDIENTS: ACETIC ACID; BENZYL ALCOHOL; ISOPROPYL ALCOHOL; LAURETH-4; WATER

Drug Facts

Active ingredient

Miconazole nitrate 2% USP

Purpose

Antifungal

Uses

- cures most athlete's foot (tinea pedis) and ringworm (tinea corporis)
- for effective relief of itchy, scaly skin between the toes

Warnings

For external use only

Flammable:

Do not use while smoking or near heat or flame.

Do not use

on children under 2 years of age unless directed by a doctor.

When using this product

- avoid contact with the eyes.
- if irritation occurs or if there is no improvement within 4 weeks, discontinue use and consult a doctor.

Keep out of reach of children.

If swallowed, get medical help or contact a Poison Control Center right away.

Directions

- clean the affected area and dry thoroughly
- apply a thin layer of the product over affected area twice daily (morning and night) or as directed by a doctor
- supervise children in the use of this product
- for athlete’s foot: pay special attention to spaces between toes; wear well-fitting, ventilated shoes and change shoes and socks at least once daily
- for athlete’s foot and ringworm, use daily for 4 weeks
- if condition persists longer, consult a doctor
- this product is not effective on scalp or nails.

Other information

- store at controlled room temperature 15-30oC (59-86oF)

Inactive ingredients

acetic acid, benzyl alcohol, isopropyl alcohol (30%), laureth-4, water

Questions or comments?

1-800-321-4576

Fungoid Tincture – 1 fl. oz. (29.57 mL) Carton

NDC0884-0293-01

PEDiNOL®

fungoid®tincture

miconazole nitrate 2%

topical antifungal

1 fl. oz. (29.57 mL)